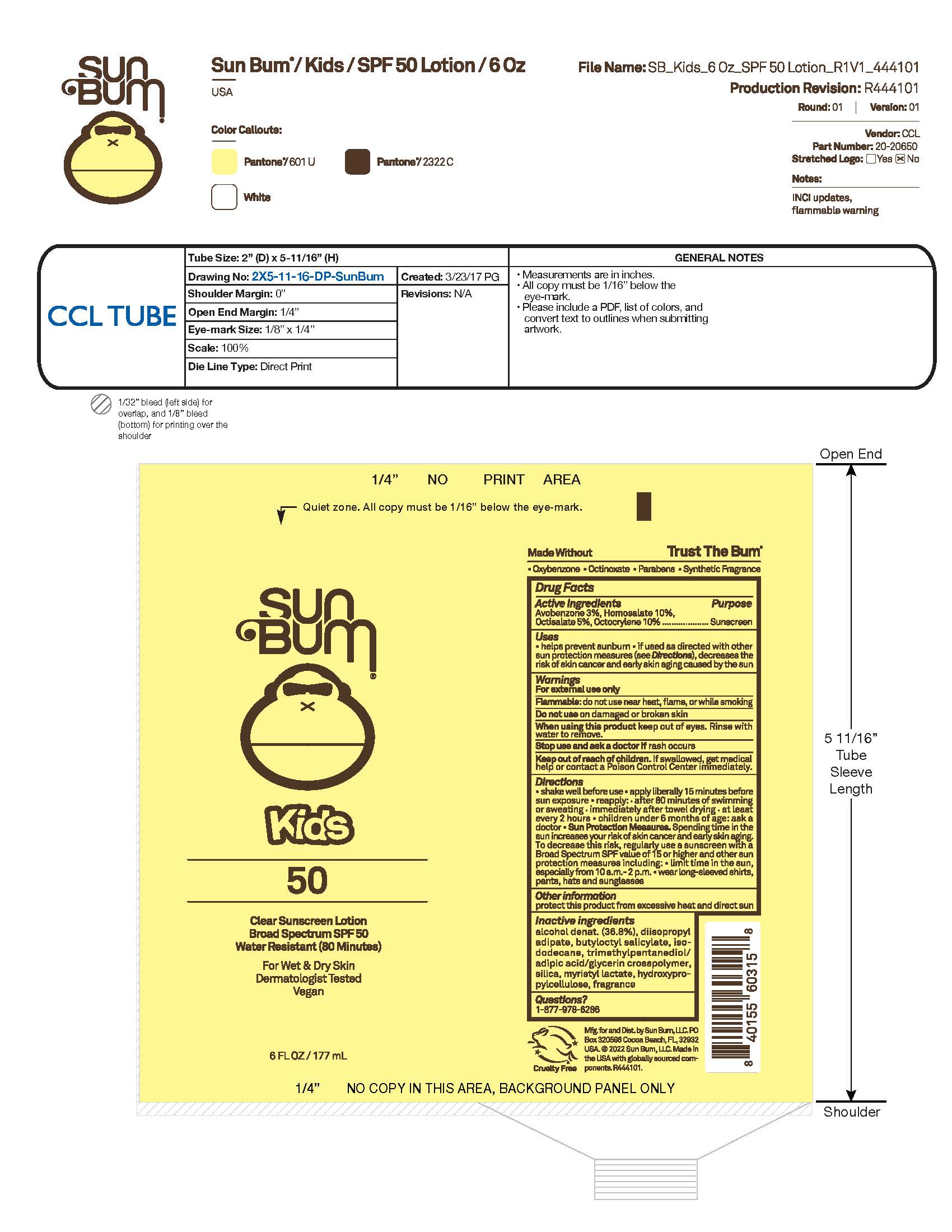 DRUG LABEL: Sun Bum Kids 50 Clear Sunscreen 6 OZ
NDC: 69039-757 | Form: LOTION
Manufacturer: Sun Bum, LLC
Category: otc | Type: HUMAN OTC DRUG LABEL
Date: 20250818

ACTIVE INGREDIENTS: OCTOCRYLENE 100 mg/1 mL; HOMOSALATE 100 mg/1 mL; AVOBENZONE 30 mg/1 mL; OCTISALATE 50 mg/1 mL
INACTIVE INGREDIENTS: SILICA; DIISOPROPYL ADIPATE; MYRISTYL LACTATE; HYDROXYPROPYLCELLULOSE; TRIMETHYLPENTANEDIOL/ADIPIC ACID/GLYCERIN CROSSPOLYMER (25000 MPA.S); BUTYLOCTYL SALICYLATE; ALCOHOL; ISODODECANE

Sun Bum Kids 50 Clear Sunscreen 6 OZ

Active Ingredients

Homosalate 10.0
Octocrylene 10.0
Octisalate 5.0
Avobenzone 3.0

Purpose

Sunscreen

Uses

• helps prevent sunburn • if used as directed with other sun protection measures, (see Directions) decreases the risk of skin cancer and early skin aging caused by the sun

Warnings

For external use only

Do not use on damaged or broken skin

When using this product keep out of eyes. Rinse with water to remove.

Stop use and ask a doctor if rash occurs

Keep out of reach of children. If swallowed, get medical help or contact a Poison Control Center immediately.

Warnings

Keep Out Of Reach Of Children

Directions

• shake well before use

• apply liberally 15 minutes before sun exposure

• reapply: • after 80 minutes of swimming or sweating • immediately after towel drying • at least every 2 hours

• children under 6 months of age: ask a doctor

• Sun Protection Measures. Spending time in the sun increases your risk of skin cancer and early skin aging. To decrease this risk, regularly use a sunscreen with a Broad Spectrum SPF value of 15 or higher and other sun protection measures including:

• limit time in the sun, especially from 10 a.m.- 2 p.m.

• wear long-sleeved shirts, pants, hats and sunglasses

Directions

• shake well before use

• apply liberally 15 minutes before sun exposure

Other Information

protect this product from excessive heat and direct sun

Inactive Ingredients

alcohol denat. (36.8%), diisopropyl adipate, isododecane, butyloctyl salicylate, silica, trimethylpentanediol/adipic acid/glycerin crosspolymer, myristyl lactate, hydroxypropylcellulose, fragrance

Questions?

1-877-978-6286